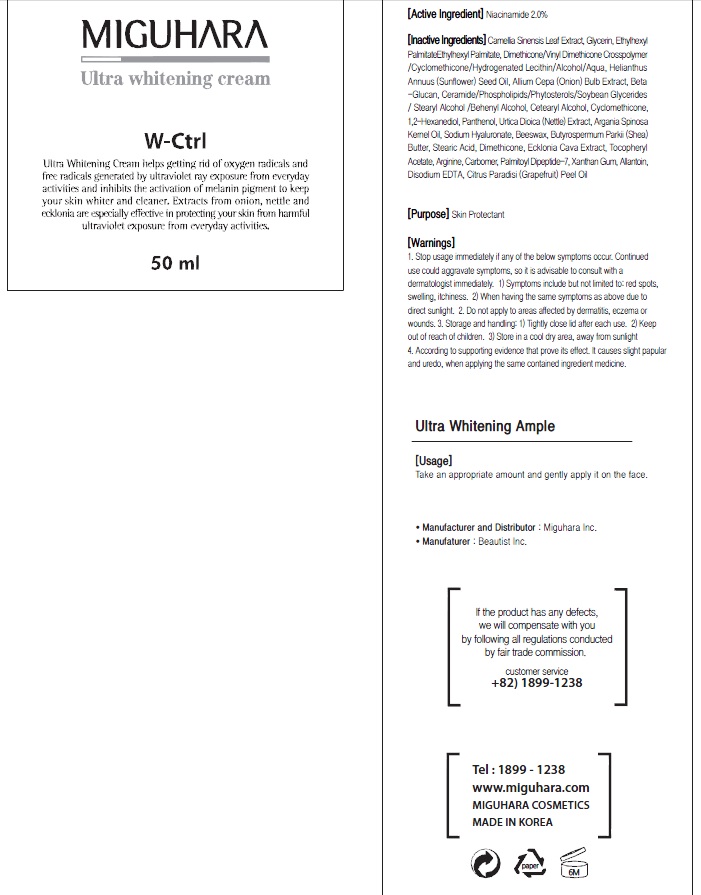 DRUG LABEL: Ultra Whitening
NDC: 70380-340 | Form: CREAM
Manufacturer: MIGUHARA
Category: otc | Type: HUMAN OTC DRUG LABEL
Date: 20160224

ACTIVE INGREDIENTS: Niacinamide 1.0 g/50 mL
INACTIVE INGREDIENTS: GREEN TEA LEAF; Glycerin

ACTIVE INGREDIENT

Active Ingredient: Niacinamide 2.0%

INACTIVE INGREDIENT

Inactive Ingredients: Camellia Sinensis Leaf Extract, Glycerin, Ethylhexyl PalmitateEthylhexyl Palmitate, Dimethicone/Vinyl Dimethicone Crosspolymer /Cyclomethicone/Hydrogenated Lecithin/Alcohol/Aqua, Helianthus Annuus (Sunflower) Seed Oil, Allium Cepa (Onion) Bulb Extract, Beta-Glucan, Ceramide/Phospholipids/Phytosterols/Soybean Glycerides/ Stearyl Alcohol /Behenyl Alcohol, Cetearyl Alcohol, Cyclomethicone, 1,2-Hexanediol, Panthenol, Urtica Dioica (Nettle) Extract, Argania Spinosa Kernel Oil, Sodium Hyaluronate, Beeswax, Butyrospermum Parkii (Shea) Butter, Stearic Acid, Dimethicone, Ecklonia Cava Extract, Tocopheryl Acetate, Arginine, Carbomer, Palmitoyl Dipeptide-7, Xanthan Gum, Allantoin, Disodium EDTA, Citrus Paradisi (Grapefruit) Peel Oil

PURPOSE

Purpose: Skin Protectant

WARNINGS

1. Stop usage immediately if any of the below symptoms occur. Continued use could aggravate symptoms, so it is advisable to consult with a dermatologist immediately. 1) Symptoms include but not limited to: red spots, swelling, itchiness. 2) When having the same symptoms as above due to direct sunlight. 2. Do not apply to areas affected by dermatitis, eczema or wounds. 3. Storage and handling: 1) Tightly close lid after each use. 2 Keep out of reach of children 3) Store in a cool dry area, away from sunlight 4. According to supporting evidence that prove its effect. It causes slight papular and uredo, when applying the same contained ingredient medicine.

KEEP OUT OF REACH OF CHILDREN

Usage

Usage: Take an appropriate amount and gently apply it on the face

Usage

Usage: Take an appropriate amount and gently apply it on the face